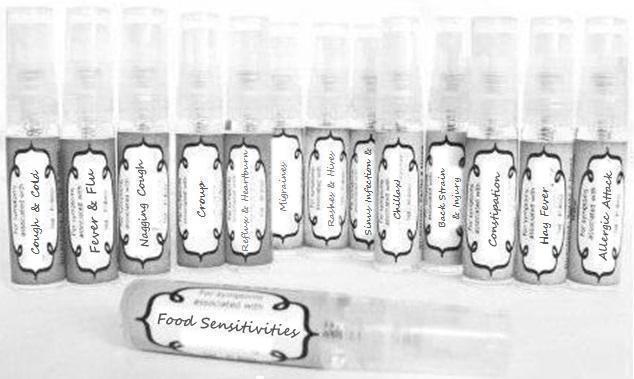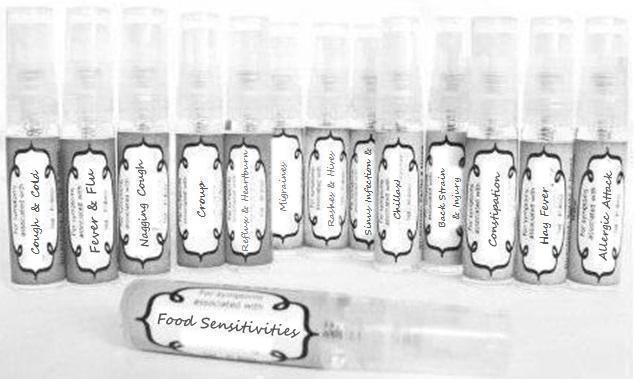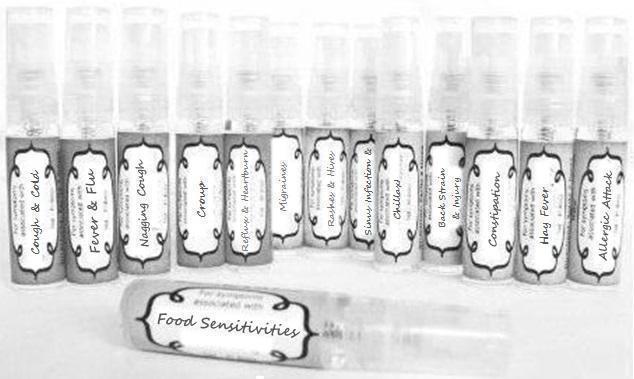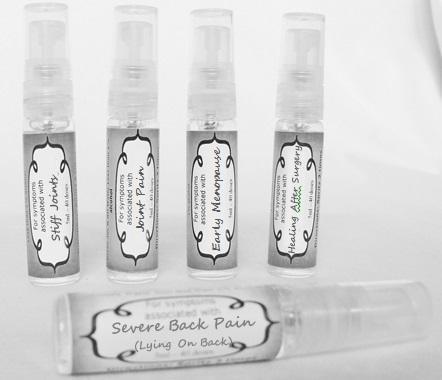 DRUG LABEL: Migraines
NDC: 59667-0024 | Form: SPRAY
Manufacturer: Home Sweet Homeopathics
Category: homeopathic | Type: HUMAN OTC DRUG LABEL
Date: 20130802

ACTIVE INGREDIENTS: ASAFETIDA 30 [hp_C]/30 [hp_C]; CANNABIS SATIVA SUBSP. INDICA TOP 30 [hp_C]/30 [hp_C]; CANNABIS SATIVA SUBSP. SATIVA FLOWERING TOP 30 [hp_C]/30 [hp_C]; ARABICA COFFEE BEAN 30 [hp_C]/30 [hp_C]; HELLEBORUS FOETIDUS ROOT 30 [hp_C]/30 [hp_C]; IPECAC 30 [hp_C]/30 [hp_C]; IRIS VERSICOLOR ROOT 30 [hp_C]/30 [hp_C]; CANIS LUPUS FAMILIARIS MILK 30 [hp_C]/30 [hp_C]; MENTHA PIPERITA 30 [hp_C]/30 [hp_C]; SODIUM SULFATE 30 [hp_C]/30 [hp_C]; CERVUS ELAPHUS HORN OIL 30 [hp_C]/30 [hp_C]; OPIUM 30 [hp_C]/30 [hp_C]; PHOSPHORIC ACID 30 [hp_C]/30 [hp_C]; SCABIES LESION LYSATE (HUMAN) 30 [hp_C]/30 [hp_C]; SANGUINARIA CANADENSIS ROOT 30 [hp_C]/30 [hp_C]; SENECIO VULGARIS 30 [hp_C]/30 [hp_C]
INACTIVE INGREDIENTS: WATER; ALCOHOL

PURPOSE

For symptoms associated with

For symptoms associated with:

To be used according to label indications.

Directions:

Spritz 1 time under the tongue 3 x per day until improvement is seen, dose once each time symptoms return.

Keep out of reach of children.

WARNINGS

If no improvement is seen after 7 days or new symptoms develop, discontinue use.

Active ingredients:

listed for each remedy.

Inactive Ingredients:

In reverse osmosis water with less than 1% alcohol.